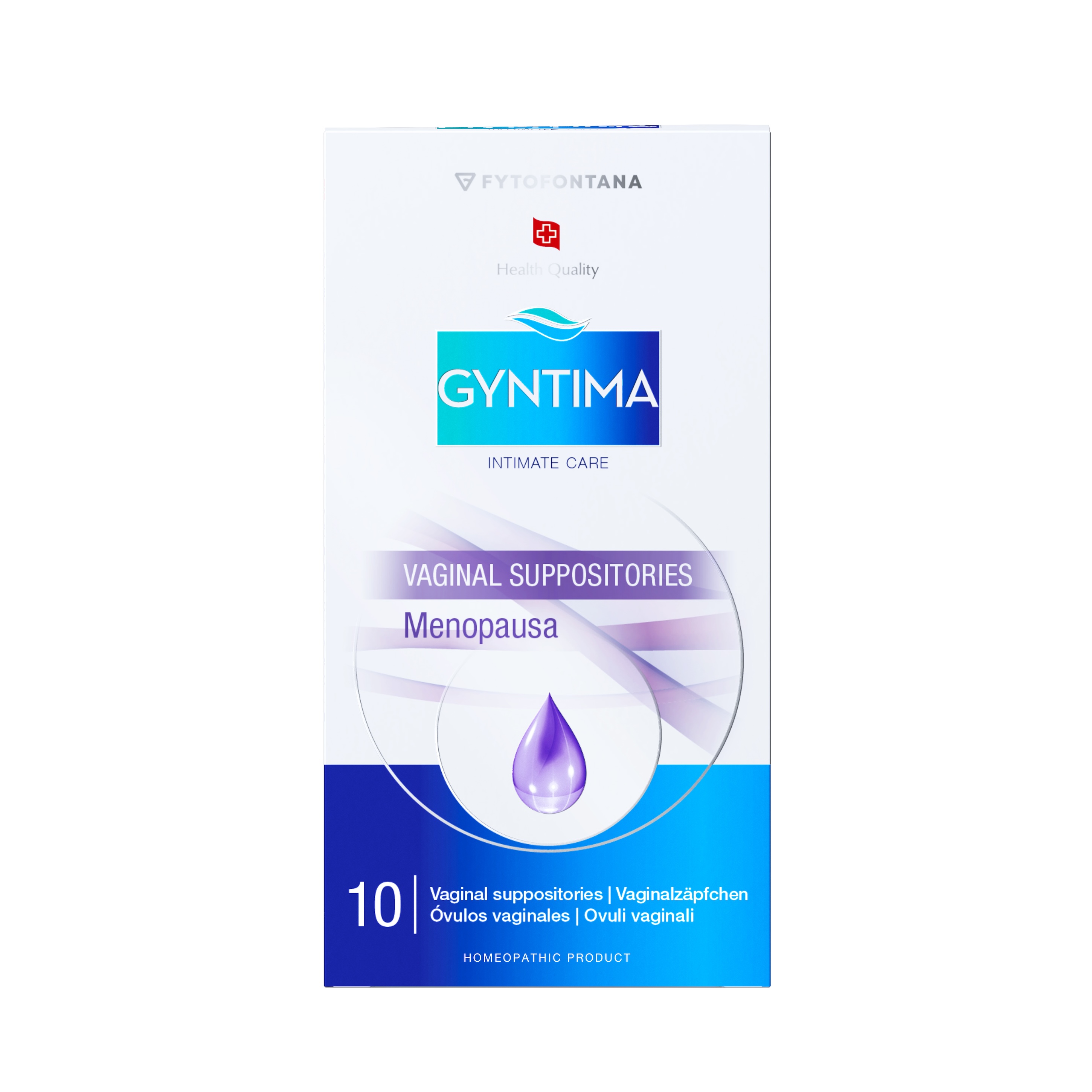 DRUG LABEL: Gyntima Menopausa
NDC: 85401-022 | Form: SUPPOSITORY
Manufacturer: Fytofontana LLC
Category: homeopathic | Type: HUMAN OTC DRUG LABEL
Date: 20250814

ACTIVE INGREDIENTS: LACTIC ACID, DL- 2 [hp_X]/1 1; SAGE 3 [hp_X]/1 1; FOLIC ACID 4 [hp_X]/1 1
INACTIVE INGREDIENTS: SOY ISOFLAVONES; POLYSORBATE 20; SODIUM CHLORIDE; MAGNESIUM SULFATE 2 [hp_X]/1 1; HYDROLYZED CASEIN (ENZYMATIC; 1000 MW); LACTOSE MONOHYDRATE; PEG-20; PEG-32

ACTIVE INGREDIENT

Acidum folicum 4X HPUS – Contributes to the regeneration and repair of vaginal tissues.
Acidum lacticum 2X HPUS – Helps regulate vaginal pH and supports microbiome balance.
Magnesii sulphas 2X HPUS – Helps soothe irritation and maintain moisture balance in vaginal tissues.
Extractum Salviae officinalis 3X HPUS – Traditionally used for its soothing properties and to support vaginal mucosal health.

PURPOSE

Acidum folicum – Supports vaginal tissue regeneration and repair.
Acidum lacticum – Regulates vaginal pH and microbiome balance.
Magnesii sulphas – Soothes irritation and maintains vaginal moisture balance.
Extractum Salviae officinalis – Supports vaginal mucosal health and soothes irritation.
Soybean Extract – Supports hydration and comfort during menopause.

INDICATIONS AND USAGE

Helps restore and maintain natural vaginal moisture levels, supporting comfort during menopause.
Supports natural hydration and helps maintain the elasticity of vaginal tissues.
Assists in relieving vaginal dryness, discomfort, itching, and sensitivity caused by hormonal changes.
Designed to support the natural balance of the vaginal microbiome and mucosa.

INACTIVE INGREDIENT

Soybean Extract, PEG 32, Lactosum, Polysorbate 20, PEG 20, Proteose Pepton, Natrii Chloridum, Sodium Hyaluronate

Directions:

Wash hands and intimate area thoroughly.
Remove the suppository from the blister pack.
Insert deeply into the vagina, preferably in the evening before bed.
Use a sanitary pad, as minor discharge may occur.

WARNINGS

For vaginal use only.
Do not use if the packaging appears damaged.
Do not use after the expiration date indicated on the packaging.
Keep out of reach of children.

Keep out of reach of children. In case of accidental ingestion, get medical help or contact a Poison Control Center right away.

ASK DOCTOR/PHARMACIST

Consult your gynecologist when using vaginal preparations along with vaginal contraceptives.
If symptoms persist after several days of use, consult your gynecologist.
After gynecological procedures, use only with a physician’s approval.
Any slight color variation or sediment is due to natural plant ingredients and does not affect product quality.

Dosage & Use

- Treatment: 1 suppository daily, preferably in the evening at bedtime, after completing the

evening hygiene routine

- Prevention: as advised by a gynecologist, depending on individual needs

Regulatory Complaince & Manufacturing Information

The active ingredients in this product are prepared in accordance with the Homeopathic Pharmacopoeia of the United States (HPUS). These uses are based on traditional homeopathic practice. They have not been reviewed by the Food and Drug Administration.

Distributed by:
Fytofontana LLC
382 NE 191st St PMB 850628
Miami, Florida 33179-3899 USA

Manufacturer:
Herb-Pharma Corporation s.r.o., 935 65 Veľké Ludince, Slovakia
Under license from Herb-Pharma AG Schweiz, Waldmannstrasse 6, 8001 Zürich, Switzerland

Storage:

Store in a cool, dry place at 5–25°C (41–77°F), away from heat sources and direct sunlight.
Shelf life: 36 months from the date of manufacture.